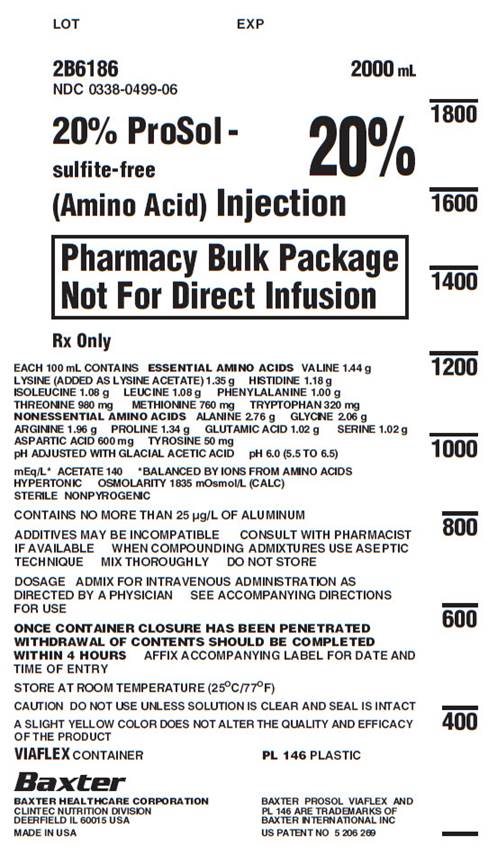 DRUG LABEL: ProSol
NDC: 0338-0499 | Form: INJECTION, SOLUTION
Manufacturer: Baxter Healthcare Corporation
Category: prescription | Type: HUMAN PRESCRIPTION DRUG LABEL
Date: 20201007

ACTIVE INGREDIENTS: VALINE 1.44 g/100 mL; LYSINE ACETATE 1.35 g/100 mL; HISTIDINE 1.18 g/100 mL; ISOLEUCINE 1.08 g/100 mL; LEUCINE 1.08 g/100 mL; PHENYLALANINE 1 g/100 mL; THREONINE 980 mg/100 mL; METHIONINE 760 mg/100 mL; TRYPTOPHAN 320 mg/100 mL; ALANINE 2.76 g/100 mL; GLYCINE 2.06 g/100 mL; ARGININE 1.96 g/100 mL; PROLINE 1.34 g/100 mL; GLUTAMIC ACID 1.02 g/100 mL; SERINE 1.02 g/100 mL; ASPARTIC ACID 600 mg/100 mL; TYROSINE 50 mg/100 mL
INACTIVE INGREDIENTS: ACETIC ACID; NITROGEN; WATER

HIGHLIGHTS OF PRESCRIBING INFORMATION

These highlights do not include all the information needed to use PROSOL safely and effectively. See full prescribing information for PROSOL.
PROSOL (amino acids) injection, for intravenous use
Initial U.S. Approval: 1998

RECENT MAJOR CHANGES

Dosage and Administration, Preparation Instructions for
Admixing Using a Parenteral Nutrition Container (2.3) 09/2020

1 INDICATIONS AND USAGE

- PROSOL is indicated as a source of amino acids for patients requiring parenteral nutrition when oral or enteral nutrition is not possible, insufficient, or contraindicated. PROSOL may be used to treat negative nitrogen balance in patents. (1)

2 DOSAGE AND ADMINISTRATION

- Pharmacy Bulk Package. Not for direct intravenous infusion. (2.1)
- See full prescribing information for information on preparation, administration, instructions for use, dosing considerations, including the recommended dosage in adults and pediatrics, and dosage modifications in patients with renal impairment. (2.1, 2.2, 2.3, 2.4, 2.5, 2.6, 2.7, 2.8)
- Protect the admixed parenteral nutrition solution from light. (2.3)

3 DOSAGE FORMS AND STRENGTHS

- Injection: 20% (0.2 grams/mL), 20 grams of amino acids per 100 mL in 2000 mL flexible containers. (3)

4 CONTRAINDICATIONS

- Known hypersensitivity to one or more amino acids (4)
- Inborn errors of amino acid metabolism (4)
- Patients with pulmonary edema or acidosis due to low cardiac output (4)

5 WARNINGS AND PRECAUTIONS

- Pulmonary Embolism due to Pulmonary Vascular Precipitates: if signs of pulmonary distress occur, stop the infusion and initiate a medical evaluation. (5.1)
- Hypersensitivity Reactions: monitor for signs and symptoms and discontinue infusion if reactions occur. (5.2)
- Risk of Infections, Refeeding Complications, and Hyperglycemia or Hyperosmolar Hyperglycemic State: monitor for signs and symptoms; monitor laboratory parameters. (5.3, 5.4, 5.5)
- Vein Damage and Thrombosis: solutions with osmolarity of 900 mOsmol/L or more must be infused through a central catheter. (2.2, 5.6)
- Hepatobiliary Disorders: monitor liver function parameters and ammonia levels. (5.7)
- Aluminum Toxicity: increased risk in patients with renal impairment, including preterm infants. (5.8, 8.4)
- Parenteral Nutrition Associated Liver Disease: increased risk in patients who receive parenteral nutrition for extended periods of time, especially preterm infants; monitor liver function tests, if abnormalities occur consider discontinuation or dosage reduction. (5.9, 8.4)
- Electrolyte Imbalance and Fluid Overload: patients with cardiac insufficiency or renal impairment may require adjustment of fluid, protein and electrolyte content. (5.10, 8.4)

6 ADVERSE REACTIONS

Adverse reactions include pulmonary vascular emboli, hypersensitivity reactions infection, refeeding syndrome, hyperglycemia and hyperosmolar hyperglycemic state, vein thrombosis, elevated liver function tests, hyperammonemia, electrolyte imbalances, and hypervolemia. (6)

To report SUSPECTED ADVERSE REACTIONS, contact Baxter Healthcare Corporation at 1-866-888-2472 or FDA at 1-800-FDA-1088 or www.fda.gov/medwatch.

8 USE IN SPECIFIC POPULATIONS

Pediatric Use: increased risk of hypoglycemia/hyperglycemia: monitor serum glucose concentrations. (8.4)

FULL PRESCRIBING INFORMATION

1 INDICATIONS AND USAGE

PROSOL is indicated as a source of amino acids for patients requiring parenteral nutrition when oral or enteral nutrition is not possible, insufficient, or contraindicated. PROSOL may be used to treat negative nitrogen balance in patients.

2 DOSAGE AND ADMINISTRATION

2.1 Important Preparation Information

PROSOL is supplied as a pharmacy bulk package for admixing only and is not for direct intravenous infusion. Prior to administration, PROSOL must be transferred to a separate parenteral nutrition container, diluted and used as an admixture with or without dextrose, electrolytes and/or lipid emulsion.

- The key factor in preparation is careful aseptic technique to avoid inadvertent touch contamination during mixing of solutions and addition of other nutrients.
- Do not remove container from overpouch until ready to use.
- Tear protective overpouch across top at slit and remove solution container. Small amounts of moisture may be found on the solution container from water permeating from inside the container. The amount of permeated water is insufficient to affect the solution significantly. If larger amounts of water are found, the container should be checked for tears or leaks.
- Inspect PROSOL prior to use. Some opacity of the plastic due to moisture absorption during the sterilization process may be observed. This is normal and does not affect the solution quality or safety. The opacity will diminish gradually. Amino acid crystals may be present. Crystals will re-dissolve upon dilution during admixture compounding.
Evaluate the following:
  1. If the outlet port protector is damaged, detached, or not present, discard container as solution path sterility may be impaired.
  2. Check to ensure the solution is clear, colorless or slightly yellow. Discard if the solution is bright yellow or yellowish brown.
  3. Check for minute leaks by squeezing inner container. If leaks are found, discard container.
- PROSOL is intended for use in the preparation of sterile, intravenous admixtures. Because additives may be incompatible with PROSOL, evaluate all additions for compatibility.

2.2 Administration Instructions

PROSOL is for admixing use only. It is not for direct intravenous infusion. Prior to administration, PROSOL must be diluted with other compatible intravenous fluids or used as an admixture with or without dextrose, electrolytes and/or lipid emulsion.

- PROSOL is to be used only in a suitable work area such as a laminar flow hood (or an equivalent clean air compounding area). The key factor in the preparation is careful aseptic technique to avoid inadvertent touch contamination during mixing of solutions and addition of other nutrients.
- PROSOL is for admixing with dextrose injection and/or lipid emulsions using a parenteral nutrition container.
- When PROSOL is admixed with dextrose injection and/or lipid emulsion, the choice of a central or peripheral venous route should depend on the osmolarity of the final infusate. Solutions with greater than 5% dextrose or with osmolarity of 900 mOsm/L or greater must be infused through a central venous catheter [see Warnings and Precautions (5.6)].
- Use a dedicated line for parenteral nutrition solutions.
- Intravenous lipid emulsions can be infused concurrently into the same vein as PROSOL -dextrose solutions by a Y-connector located near the infusion site; flow rates of each solution should be controlled separately by infusion pumps.
- For administration without lipid emulsion, use a 0.22 micron in-line filter. If lipid emulsion is also administered, use a 1.2 micron in-line filter.
- To prevent air embolism, use a non-vented infusion set or close the vent on a vented set, avoid multiple connections, do not connect flexible containers in series, fully evacuate residual gas in the container prior to administration, do not pressurize the flexible container to increase flow rates, and if administration is controlled by a pumping device, turn off pump before the container runs dry.
- If admixed or infused with lipid emulsion, do not use administration sets and lines that contain di-2-ethylhexyl phthalate (DEHP). Administration sets that contain polyvinyl chloride (PVC) components have DEHP as a plasticizer.
- Calcium and phosphate ratios must be considered. Excess addition of calcium and phosphate, especially in the form of mineral salts, may result in the formation of calcium phosphate precipitates [see Warnings and Precautions (5.1)].
- Prior to infusion, visually inspect the diluted parenteral nutrition solution containing PROSOL for particulate matter. The solution should be clear and there should be no precipitates. A slight yellow color does not alter the quality and efficacy of this product. If lipid has been added, ensure the emulsion has not separated. Separation of the emulsion can be visibly identified by a yellowish streaking or the accumulation of yellowish droplets in the mixed emulsion. Discard the admixture if any of the above are observed.

2.3 Preparation Instructions for Admixing Using a Parenteral Nutrition Container

- Open by tearing protective overwrap across top at slit and remove solution container. If overpouch has been previously opened or is damaged, discard solution.
- If the outlet port protector is damaged, detached, or not present, discard the container.
- Some opacity of the plastic due to moisture absorption during the sterilization process may be observed.
- Check for minute leaks by squeezing the inner container firmly. If leaks are found, discard solution.
- Once the protective foil overwrap has been removed, suspend container from eyelet support.
- Remove plastic protector from outlet port at bottom of container.
- Attach solution transfer set. Refer to complete directions accompanying set. Note: The closure shall be penetrated only one time with a suitable sterile transfer device or dispensing set which allows measured dispensing of the contents.
- Prepare the admixture into the parenteral nutrition container using strict aseptic techniques to avoid microbial contamination.
- Do not add the lipid emulsion to the parenteral nutritional container first; destabilization of the lipid emulsion may occur from such an admixture.
- PROSOL may be mixed with dextrose injection and/or lipid emulsion. The following proper mixing sequence must be followed to minimize pH related problems by ensuring that typically acidic dextrose injections are not mixed with lipid emulsions alone:
  1. Transfer dextrose injection to the parental nutrition container.
  2. Transfer PROSOL to the parenteral nutrition container.
  3. Transfer lipid emulsion to the parenteral nutrition container.
- Because additives may be incompatible, evaluate all additions to the parenteral nutrition container for compatibility and stability of the resulting preparation. Consult with pharmacist, if available. Questions about compatibility may be directed to Baxter. If it is deemed advisable to introduce additives to the parenteral nutrition container, use aseptic technique.
- Use gentle agitation during admixing to minimize localized concentration effects; shake containers gently after each addition.
- Alternatively, simultaneous transfer to the parenteral nutrition container of PROSOL, dextrose injection and lipid emulsion is also permitted.
- For admixing using an automated device, refer to Instructions for Use for the applicable device.
- The prime destabilizers of emulsions are excessive acidity (such as pH below 5) and inappropriate electrolyte content. Give careful consideration to additions of divalent cations (Ca++ and Mg++), which have been shown to cause emulsion instability. Amino acid solutions exert buffering effects that protect the emulsion.
- Inspect the final parenteral nutrition solution containing PROSOL to ensure that:
  - Precipitates have not formed during the mixing or addition of additives.
  - The emulsion has not separated. Separation of the emulsion can be visibly identified by a yellowish streaking or the accumulation of yellowish droplets in the admixed emulsion.
  - Discard the admixture if any of the above are observed.
- Containers should not be written on directly since ink migration has not been investigated. Affix accompanying label for date and time of entry.
Stability and Storage
- Use for admixing should be limited to up to 4 hours at room temperature (25ºC/77ºF) after the container closure has been penetrated.
- Admixtures should be used promptly with storage under refrigeration 2° to 8°C (36° to 46°F) not to exceed 24 hours and must be completely used within 24 hours after removal from refrigeration. Any mixture remaining must be discarded.
- Protect the admixed parenteral nutrition solution from light.
- For single use only. Discard used container of PROSOL.

2.4 Dosing Considerations

- PROSOL is for admixing only. It is not for direct intravenous infusion. Prior to administration, PROSOL must be diluted with other compatible intravenous fluids or used as an admixture with or without dextrose, electrolytes and lipid emulsion.
- PROSOL is a part of the parenteral nutrition regimen which also includes dextrose, electrolytes, and lipid emulsion. Protein, caloric, fluid and electrolyte requirements all need to be taken into consideration when determining individual patient dosage needs.
- The dosage of the final parenteral nutrition solution containing PROSOL must be based on the concentrations of all components in the solution and the recommended nutritional requirements [see Dosage and Administration (2.5, 2.6, 2.7)]. Consult the prescribing information of all added components to determine the recommended nutritional requirements for dextrose and lipid emulsion, as applicable.
- The dosage of PROSOL should be individualized based on the patient’s clinical condition (ability to adequately metabolize amino acids), body weight and nutritional/fluid requirements, as well as additional energy given orally/enterally to the patient. Prior to initiating parenteral nutrition, the following patient information should be reviewed: review of all medications, gastrointestinal function and laboratory data (such as electrolytes (including magnesium, calcium, and phosphorus), glucose, urea/creatinine, liver panel, complete blood count and triglyceride level (if adding lipid emulsion)).
- Lipid emulsion administration should be considered with prolonged use (more than 5 days) of parenteral nutrition and is required in order to prevent essential fatty acid deficiency (EFAD). Serum lipids should be monitored for evidence of EFAD in patients maintained on fat-free parenteral nutrition. See complete prescribing information of lipid emulsion.
- Prior to administration of parenteral nutrition solution containing PROSOL, correct severe fluid, electrolyte and acid-base disorders.
- In many patients, provision of adequate calories in the form of hypertonic dextrose may require the administration of exogenous insulin to prevent hyperglycemia and glycosuria.
- Monitor levels of serum potassium during parenteral nutrition therapy. It may be necessary to add additional potassium to the parenteral nutrition admixture.

2.5 Recommended Dosage in Adults

The recommended adult daily dosage of PROSOL and the nutritional requirements for protein (nitrogen) are shown inTable 1.

As a component of parenteral nutrition, PROSOL provides 0.2 g protein/mL, which corresponds to 0.032 g nitrogen/mL.

As indicated on an individual basis, vitamins, electrolytes, trace elements and other components (including dextrose, electrolytes and lipid emulsion) can be added to the parenteral nutrition solution to meet nutrient needs and prevent deficiencies and complications from developing.

A maximum fluid supply of 40 mL/kg/day of parenteral nutrition solution, based on protein, should not be exceeded in adult patients; this volume does not take carbohydrates or electrolytes into consideration.

Table 1. Recommended Daily Dosage in Adults
Adult Patient Population | Recommended Protein Requirement (g/kg/day)1 | Corresponding Nitrogen Requirement (g/kg/day) | Recommended Daily Dosage of PROSOL (mL/kg/day) [A maximum fluid supply of 40 mL/kg/day of parenteral nutrition solution should not be exceeded in adult patients.]
Stable Patients | 0.8 to 1.0 | 0.13 to 0.16 | 4 to 5
Critically Ill Patients [Includes patients requiring more than 2 to 3 days in the intensive care unit with organ failure, sepsis or postoperative major surgery. Do not use in patients with conditions that are contraindicated [see Contraindications (4)].] | 1.5 to 2.0 | 0.24 to 0.32 | 7.5 to 10

The flow rate of the parenteral nutrition solution must be adjusted taking into account the dose being administered, the daily volume intake, and the duration of the infusion. The flow rate should be increased gradually and governed, especially during the first few days of therapy, by the patient’s tolerance to dextrose. Daily intake of PROSOL and dextrose should be increased gradually to the maximum required dose as indicated by frequent determinations of blood glucose levels.

2.6 Dosage Modifications in Patients with Renal Impairment

Prior to administration, correct severe fluid or electrolyte imbalances. Closely monitor serum electrolyte levels and adjust the volume of parenteral nutrition administered as required [see Warnings and Precautions (5.10)].

Patients with renal impairment not needing dialysis require 0.6 to 0.8 g of protein/kg/day. Serum electrolyte levels should be closely monitored. Patients on hemodialysis or continuous renal replacement therapy should receive 1.2 to 1.8 g of protein/kg/day up to a maximum of 2.5 g of protein/kg/day based on nutritional status and estimated protein losses.^2

2.7 Recommended Dosage in Pediatric Patients

The dosage and constant infusion rate of intravenous dextrose must be selected with caution in pediatric patients, particularly neonates and low weight infants, because of the increased risk of hyperglycemia/hypoglycemia [see Use in Specific Populations (8.4)]. Frequent monitoring of serum glucose concentrations is required when dextrose is prescribed to pediatric patients, particularly neonates and low birth weight infants. The infusion rate and volume should be determined by the consulting physician experienced in pediatric intravenous fluid therapy.

In pediatric patients, PROSOL is dosed on the basis of protein provided as amino acids. The recommended dosage, by age group is provided in Table 2.

Infusion rates are based on protein and do not take carbohydrates, fluid or electrolytes into consideration.

PROSOL does not contain the amino acids cysteine and taurine, considered conditionally essential for neonates and infants. If possible, these amino acids should be added to the parenteral nutrition admixtures if used in this pediatric population.

Table 2. Recommended Daily Dosage in Pediatrics Patients
Age | Recommended Protein [Protein is provided as amino acids. When infused intravenously, amino acids are metabolized and utilized as the building blocks of protein.] Requirement (g/kg/day)^1 | Corresponding Nitrogen Requirement (g/kg/day) | Recommended Daily Dosage of PROSOL (mL/kg/day)
Preterm and term infants less than 1 month of age | 3 to 4 | 0.48 to 0.64 | 15 to 20
Pediatric patients > 1 month to 1 year of age | 2 to 3 | 0.32 to 0.48 | 10 to 15
Pediatric patients 1 to 10 years of age | 1 to 2 | 0.16 to 0.32 | 5 to 10
Pediatric patients 11 to 17 years of age | 0.8 to 1.5 | 0.13 to 0.24 | 4 to 7.5

2.8 Discontinuation of Parenteral Nutrition

To reduce the risk of hypoglycemia after discontinuation, a gradual decrease in flow rate in the last hour of infusion should be considered when administering parenteral nutrition solutions containing dextrose.

3 DOSAGE FORMS AND STRENGTHS

PROSOL 20% is a sterile solution of 20 grams of amino acids per 100 mL (0.2 gram/mL) available in 2000 mL flexible containers. Table 3 describes the individual components of PROSOL.

Table 3. Ingredients per 100 mL of PROSOL
Amino Acids | 20.0 g
Total Nitrogen | 3.21 g
Essential Amino Acids
Valine | 1.44 g
Lysine (added as Lysine Acetate) | 1.35 g
Histidine | 1.18 g
Isoleucine | 1.08 g
Leucine | 1.08 g
Phenylalanine | 1.00 g
Threonine | 980 mg
Methionine | 760 mg
Tryptophan | 320 mg
Nonessential Amino Acids
Alanine | 2.76 g
Glycine | 2.06 g
Arginine | 1.96 g
Proline | 1.34 g
Glutamic Acid | 1.02 g
Serine | 1.02 g
Aspartic Acid | 600 mg
Tyrosine | 50 mg
Anion profiles per liter [Balanced by ions from amino acids.]
Acetate from Lysine Acetate and glacial acetic acid [Derived from pH adjustment with glacial acetic acid.] | 140 mEq
pH (Range); pH adjusted with glacial acetic acid | 6.0 (5.5 to 6.5)
Osmolarity (calc.) | 1835 mOsmol/L

4 CONTRAINDICATIONS

The use of PROSOL is contraindicated in:

- Patients with known hypersensitivity to one or more amino acids [see Warnings and Precautions (5.2)].
- Patients with inborn errors of amino acid metabolism due to risk of severe metabolic or neurologic complications.
- Patients with pulmonary edema or acidosis due to low cardiac output.

5 WARNINGS AND PRECAUTIONS

5.1 Pulmonary Embolism due to Pulmonary Vascular Precipitates

Pulmonary vascular precipitates causing pulmonary vascular emboli and pulmonary distress have been reported in patients receiving parenteral nutrition. In some cases, fatal outcomes due to pulmonary embolism have occurred. PROSOL contains no added phosphorus. Patients, especially those with hypophosphatemia, may require the addition of phosphate. To prevent hypocalcemia, calcium supplementation should always accompany phosphate administration. Excessive addition of calcium and phosphate increases the risk of the formation of calcium phosphate precipitates. Precipitates have been reported even in the absence of phosphate salt in the solution. Precipitation following passage through an in-line filter and suspected in vivo precipitate formation has also been reported. If signs of pulmonary distress occur, stop the infusion and initiate a medical evaluation. In addition to inspection of the solution [see Dosage and Administration (2.1, 2.2, 2.3, 2.4)], the infusion set and catheter should also periodically be checked for precipitates.

5.2 Hypersensitivity Reactions

Hypersensitivity reactions including anaphylaxis have been reported with parenteral nutrition solutions containing PROSOL. Stop the infusion immediately and treat patient accordingly if any signs or symptoms of a hypersensitivity reaction develop. Signs or symptoms may include: hypotension, hypertension, peripheral cyanosis, tachycardia, dyspnea, vomiting, nausea, urticaria, rash, pruritus, erythema, hyperhidrosis, pyrexia, and chills.

5.3 Risk of Infections

Patients who require parenteral nutrition are at high risk of infections because the nutritional components of these solutions can support microbial growth. Infection and sepsis may also occur as a result of the use of intravenous catheters to administer parenteral nutrition.

The risk of infection is increased in patients with malnutrition-associated immunosuppression, hyperglycemia exacerbated by dextrose infusion, long-term use and poor maintenance of intravenous catheters, or immunosuppressive effects of other concomitant conditions, drugs, or other components of the parenteral formulation (e.g., lipid emulsion).

To decrease the risk of infection, ensure aseptic technique in catheter placement and maintenance, as well as aseptic technique in the preparation and administration of the nutritional formula.

Monitor for signs and symptoms (including fever and chills) of early infections, including laboratory test results (including leukocytosis and hyperglycemia) and frequent checks of the parenteral access device and insertion site for edema, redness and discharge.

5.4 Refeeding Syndrome

Refeeding severely undernourished patients may result in refeeding syndrome, characterized by the intracellular shift of potassium, phosphorus, and magnesium as the patient becomes anabolic. Thiamine deficiency and fluid retention may also develop. To prevent these complications, monitor severely undernourished patients and slowly increase nutrient intakes.

5.5 Hyperglycemia or Hyperosmolar Hyperglycemic State

Administration of parenteral nutrition solutions containing dextrose in patients with diabetes mellitus, impaired glucose tolerance may worsen hyperglycemia. Administration of dextrose at a rate exceeding the patient’s utilization rate may lead to hyperglycemia, coma, and death. Patients with underlying confusion and renal impairment who receive dextrose infusions, may be at greater risk of developing hyperosmolar hyperglycemic state. Monitor blood glucose levels and treat hyperglycemia to maintain optimum levels while administering parenteral nutrition solutions containing dextrose. Insulin may be administered or adjusted to maintain optimal blood glucose levels during administration of parenteral nutrition solutions containing dextrose.

5.6 Vein Damage and Thrombosis

PROSOL must be diluted and used as an admixture with or without dextrose, electrolytes and/or lipid emulsion. It is not for direct intravenous infusion. Solutions containing more than 5% dextrose or with an osmolarity of 900 mOsmol/L or greater must be infused through a central catheter [see Dosage and Administration (2.2)]. The infusion of hypertonic nutrient injections into a peripheral vein may result in vein irritation, vein damage, and/or thrombosis. The primary complication of peripheral access is venous thrombophlebitis, which manifests as pain, erythema, tenderness or a palpable cord. Remove the catheter as soon as possible, if thrombophlebitis develops.

5.7 Hepatobiliary Disorders

Hepatobiliary disorders are known to develop in some patients without preexisting liver disease who receive parenteral nutrition, including cholecystitis, cholelithiasis, cholestasis, hepatic steatosis, fibrosis and cirrhosis, possibly leading to hepatic failure. The etiology of these disorders is thought to be multifactorial and may differ between patients.

Increase in blood ammonia levels and hyperammonemia may occur in patients receiving amino acid solutions, including PROSOL. In some patients, this may indicate hepatic insufficiency or the presence of an inborn error of amino acid metabolism [see Contraindications (4), Use in Specific Populations (8.4)].

Monitor liver function parameters and ammonia levels. Patients developing signs of hepatobiliary disorders should be assessed early by a clinician knowledgeable in liver diseases in order to identify possible causative and contributory factors, and possible therapeutic and prophylactic interventions.

5.8 Aluminum Toxicity

PROSOL contains no more than 25 mcg/L of aluminum. However, with prolonged parenteral administration in patients with renal impairment, the aluminum contained in PROSOL may reach toxic levels. Preterm infants are at a greater risk because their kidneys are immature, and they require large amounts of calcium and phosphate solutions, which contain aluminum.

Patients with renal impairment, including preterm infants, who receive parenteral levels of aluminum at greater than 4 to 5 mcg/kg/day, accumulate aluminum at levels associated with central nervous system and bone toxicity. Tissue loading may occur at even lower rates of administration.

5.9 Risk of Parenteral Nutrition Associated Liver Disease

Parenteral Nutrition Associated Liver Disease (PNALD) has been reported in patients who receive parenteral nutrition for extended periods of time, especially preterm infants, and can present as cholestasis or steatohepatitis. The exact etiology is unknown and is likely multifactorial. If patients treated with parenteral nutrition solutions containing PROSOL develop liver test abnormalities, consider discontinuation or dosage reduction.

5.10 Electrolyte Imbalance and Fluid Overload

Patients with renal impairment, such as pre-renal azotemia, renal obstruction, and protein-losing nephropathy may be at increased risk of electrolyte and fluid volume imbalance. Patients with cardiac insufficiency and pulmonary congestion are susceptible to excess fluid accumulation. Use parenteral nutrition solutions containing PROSOL with caution in patients with cardiac insufficiency or renal impairment. The dosage of parenteral nutrition may require adjustment with specific attention to fluid, protein, and electrolyte content in these patients.

Monitor renal function parameters. Patients developing signs of renal impairment should be assessed early by a clinician knowledgeable in renal disease in order to determine the appropriate parenteral nutrition dosage and other treatment options.

5.11 Monitoring/Laboratory Tests

Monitor fluid and electrolyte status, serum osmolarity, blood glucose, liver and kidney function, blood count and coagulation parameters throughout treatment. If electrolyte levels are severely elevated, stop parenteral nutrition containing PROSOL until levels have been corrected.

6 ADVERSE REACTIONS

The following serious adverse reactions are discussed in greater detail in other sections of the prescribing information.

- Pulmonary embolism due to pulmonary vascular precipitates [see Warnings and Precautions (5.1)]
- Hypersensitivity reactions [see Warnings and Precautions (5.2)]
- Risk of infections [see Warnings and Precautions (5.3)]
- Refeeding syndrome [see Warnings and Precautions (5.4)]
- Hyperglycemia or hyperosmolar hyperglycemic state [see Warnings and Precautions (5.5)]
- Vein damage and thrombosis [see Warnings and Precautions (5.6)]
- Hepatobiliary disorders [see Warnings and Precautions (5.7)]
- Aluminum toxicity [see Warnings and Precautions (5.8)]
- Parenteral Nutrition Associated Liver Disease [see Warnings and Precautions (5.9)]
- Electrolyte imbalance and fluid overload [see Warnings and Precautions (5.10)]

The following adverse reactions from voluntary reports or clinical studies have been reported with parenteral amino acid products. Because many of these reactions were reported voluntarily from a population of uncertain size, it is not always possible to reliably estimate their frequency or establish a causal relationship to drug exposure.

- Metabolic acidosis
- Alkalosis
- Osmotic diuresis and dehydration
- Rebound hypoglycemia
- Hypo- and hyper-vitaminosis

8 USE IN SPECIFIC POPULATIONS

8.1 Pregnancy

Risk Summary

Limited published data with injectable amino acids solutions, including PROSOL in pregnant women are not sufficient to inform a drug associated risk for adverse developmental outcomes. However, malnutrition in pregnant women is associated with adverse maternal and fetal outcomes [see Clinical Considerations]. Animal reproduction studies have not been conducted with injectable amino acids solutions, including PROSOL.

The background risk of major birth defects and miscarriage for the indicated population is unknown. All pregnancies have a background risk of birth defect, loss, or other adverse outcomes. However, the background risk in the U.S. general population of major birth defects is 2 to 4% and of miscarriage is 15 to 20% of clinically recognized pregnancies.

Clinical Considerations

Disease-Associated Maternal and/or Embryo-Fetal Risk

Severe malnutrition in pregnant women is associated with preterm delivery, low birth weight, intrauterine growth restriction, congenital malformations and perinatal mortality. Parenteral nutrition should be considered if a pregnant woman’s nutritional requirements cannot be fulfilled by oral or enteral intake.

8.2 Lactation

Risk Summary

There are no data available to assess the presence of injectable amino acids, including PROSOL in human milk, the effects of PROSOL on the breastfed infant or the effects on milk production. The lack of clinical data during lactation precludes a clear determination of the risk of PROSOL to a child during lactation; therefore, the developmental and health benefits of breastfeeding should be considered along with the mother’s clinical need for PROSOL and any potential adverse effects on the breastfed child from PROSOL or from the underlying maternal condition.

8.4 Pediatric Use

Neonates, especially premature infants with low birth weight, are at increased risk of developing hypo- or hyperglycemia and therefore need close monitoring during treatment with intravenous glucose solutions to ensure adequate glycemic control in order to avoid potential long term adverse effects [see Dosage and Administration (2.7)].

Plasma electrolyte concentrations should be closely monitored in the pediatric patients who may have impaired ability to regulate fluids and electrolytes.

Hyperammonemia is of special significance in infants (birth to two years). This reaction appears to be related to a deficiency of the urea cycle amino acids of genetic or product origin. It is essential that blood ammonia be measured frequently in infants [see Warnings and Precautions (5.7)].

Because of immature renal function, preterm infants receiving prolonged parenteral nutrition treatment with PROSOL may be at risk of aluminum toxicity [see Warnings and Precautions (5.8)].

Patients, including pediatric patients, may be at risk for PNALD [see Warnings and Precautions (5.9)].

8.5 Geriatric Use

Clinical studies with PROSOL have not been performed to determine whether subjects aged 65 and over respond differently from other younger subjects. Other reported clinical experience has not identified differences in responses between the elderly and younger patients.

In general, dose selection for an elderly patient should be cautious, usually starting at the low end of the dosing range, reflecting the greater frequency of decreased hepatic, renal, or cardiac function, and of concomitant disease or drug therapy.

8.6 Renal Impairment

In patients with impaired renal function, parenteral nutrition solutions containing PROSOL should be administered with caution. Frequent clinical evaluation and laboratory tests to monitor renal function such as serum electrolytes (especially phosphate and potassium) and fluid balance should be conducted [see Dosage and Administration (2.6), and Warnings and Precautions (5.10)].

8.7 Hepatic Impairment

In patients with impaired liver function, parenteral nutrition solutions containing PROSOL should be administered starting at the low end of the dosing range [see Dosage and Administration (2.5)]. Frequent clinical evaluation and laboratory tests to monitor liver function such as bilirubin and liver function parameters should be conducted [see Warnings and Precautions (5.7)].

10 OVERDOSAGE

An increased infusion rate of parenteral nutrition can cause hypervolemia, electrolyte disturbances, acidosis and/or azotemia, hyperglycemia, hyperosmolality [see Warnings and Precautions (5.5, 5.10)].

Severe hyperglycemia and severe dilutional hyponatremia, and their complications, can be fatal.

Discontinue infusion and institute appropriate corrective measures in the event of overhydration or solute overload during therapy, with particular attention to respiratory and cardiovascular systems.

For current information on the management of poisoning or overdosage, contact the National Poison Control Center at 1-800-222-1222 or www.poison.org.

11 DESCRIPTION

PROSOL 20% (amino acids) injection is a sterile, nonpyrogenic, hypertonic solution of essential and nonessential amino acids supplied in a flexible container as a Pharmacy Bulk Package. A Pharmacy Bulk Package is a container of a sterile preparation for parenteral use that contains many single doses. The contents are intended for use in a pharmacy admixture program [see Dosage and Administration (2.1)]. PROSOL is not for direct intravenous infusion.

The formulas for the individual amino acids found in PROSOL are provided in Table 4.

Table 4. Formulas for Amino Acids
Essential Amino Acids
Leucine | (CH3)2 CHCH2CH (NH2) COOH
Isoleucine | CH3CH2CH (CH3) CH (NH2) COOH
Lysine (added as the hydrochloride salt) | H2N (CH2)4 CH (NH2) COOH
Valine | (CH3)2 CHCH (NH2) COOH
Phenylalanine | (C6H5) CH2 CH (NH2) COOH
Histidine | (C3H3N2) CH2CH (NH2) COOH
Threonine | CH3CH (OH) CH (NH2) COO
Methionine | CH3S (CH2)2 CH (NH2) COOH
Tryptophan | (C8H6N) CH2 CH (NH2) COOH
Nonessential Amino Acids
Alanine | CH3CH (NH2) COOH
Arginine | H2NC (NH) NH (CH2)3 CH (NH2) COOH
Aspartic Acid | HOOC CH2 CH (NH2) COOH
Glutamic Acid | HOOC (CH2)2 CH (NH2) COOH
Glycine | H2NCH2COOH
Proline | [(CH2)3 NH CH] COOH
Serine | HOCH2CH (NH2) COOH
Tyrosine | [C6H4 (OH)] CH2CH (NH2) COOH

PROSOL contains no more than 25 mcg/L of aluminum.

12 CLINICAL PHARMACOLOGY

12.1 Mechanism of Action

PROSOL is used as a supplement of nutrition in patients, providing amino acids parenterally.

The amino acids provide the structural units that make up proteins and are used to synthesize proteins and other biomolecules or are oxidized to urea and carbon dioxide as a source of energy.

15 REFERENCES

1. Ayers P. et al. A.S.P.E.N. Parenteral Nutrition Handbook, 2nd ed. 2014 pg. 123
2. Mueller CM ed. The A.S.P.E.N. Nutrition Support Core Curriculum 3rd ed. 2017. Chapter 29 Sarav M, Kovesdy C. Renal Disease., pg. 565-586

16 HOW SUPPLIED/STORAGE AND HANDLING

PROSOL 20% (amino acids) injection is available in plastic Pharmacy Bulk Package flexible containers in the following size as shown in Table 5 below.

Table 5. PROSOL Dosage Form
Code | Volume | NDC Number
2B6186 | 2000 mL | NDC 0338-0499-06

Minimize exposure of PROSOL to heat and avoid excessive heat.

Protect from freezing.

Store PROSOL at room temperature (25ºC/77ºF). Brief exposure up to 40ºC/104ºF does not adversely affect the product.

Do not use if protective overpouch has been previously opened or damaged.

For storage of admixed solutions [see Dosage and Administration (2.3)].

17 PATIENT COUNSELING INFORMATION

Inform patients, caregivers, or home healthcare providers of the following risks of PROSOL:

- Pulmonary embolism due to pulmonary vascular precipitates [see Warnings and Precautions (5.1)]
- Hypersensitivity reactions [see Warnings and Precautions (5.2)]
- Risk of infections [see Warnings and Precautions (5.3)]
- Refeeding syndrome [see Warnings and Precautions (5.4)]
- Hyperglycemia or hyperosmolar hyperglycemic state [see Warnings and Precautions (5.5)]
- Vein damage and thrombosis [see Warnings and Precautions (5.6)]
- Hepatobiliary disorders [see Warnings and Precautions (5.7)]
- Aluminum toxicity [see Warnings and Precautions (5.8)]
- Parenteral Nutrition Associated Liver Disease (PNALD) [see Warnings and Precautions (5.9)]
- Electrolyte imbalance and fluid overload [see Warnings and Precautions (5.10)]

Baxter Healthcare Corporation
Deerfield, IL 60015 USA

07-19-00-3506

Baxter and Prosol are registered trademarks of Baxter International Inc.

PACKAGE/LABEL PRINCIPAL DISPLAY PANEL

Container Label

LOT EXP

2B6186 2000 mL
NDC 0338-0499-06

20% ProSol -
sulfite-free
20%

(Amino Acid) Injection

Pharmacy Bulk Package
Not For Direct Infusion

Rx Only

EACH 100 mL CONTAINS ESSENTIAL AMINO ACIDS VALINE 1.44 g
LYSINE (ADDED AS LYSINE ACETATE) 1.35 g HISTIDINE 1.18 g
ISOLEUCINE 1.08 g LEUCINE 1.08 g PHENYLALANINE 1.00 g
THREONINE 980 mg METHIONINE 760 mg TRYPTOPHAN 320 mg
NONESSENTIAL AMINO ACIDS ALANINE 2.76 g GLYCINE 2.06 g
ARGININE 1.96 g PROLINE 1.34 g GLUTAMIC ACID 1.02 g SERINE 1.02 g
ASPARTIC ACID 600 mg TYROSINE 50 mg
pH ADJUSTED WITH GLACIAL ACETIC ACID pH 6.0 (5.5 TO 6.5)

mEq/L* ACETATE 140 *BALANCED BY IONS FROM AMINO ACIDS
HYPERTONIC OSMOLARITY 1835 mOsmol/L (CALC)
STERILE NONPYROGENIC

CONTAINS NO MORE THAN 25 μg/L OF ALUMINUM

ADDITIVES MAY BE INCOMPATIBLE CONSULT WITH PHARMACIST
IF AVAILABLE WHEN COMPOUNDING ADMIXTURES USE ASEPTIC
TECHNIQUE MIX THOROUGHLY DO NOT STORE

DOSAGE ADMIX FOR INTRAVENOUS ADMINISTRATION AS
DIRECTED BY A PHYSICIAN SEE ACCOMPANYING DIRECTIONS
FOR USE

ONCE CONTAINER CLOSURE HAS BEEN PENETRATED
WITHDRAWAL OF CONTENTS SHOULD BE COMPLETED
WITHIN 4 HOURS AFFIX ACCOMPANYING LABEL FOR DATE AND
TIME OF ENTRY

STORE AT ROOM TEMPERATURE (25°C/77°F)

CAUTION DO NOT USE UNLESS SOLUTION IS CLEAR AND SEAL IS INTACT
A SLIGHT YELLOW COLOR DOES NOT ALTER THE QUALITY AND EFFICACY
OF THE PRODUCT

VIAFLEX CONTAINER

PL 146 PLASTIC

VIAFLEX CONTAINER PL 146 PLASTIC

Baxter Logo

BAXTER HEALTHCARE CORPORATION
CLINTEC NUTRITION DIVISION
DEERFIELD, IL 60015 USA

MADE IN USA

BAXTER, PROSOL, VIAFLEX AND
PL 146 ARE TRADEMARKS OF
BAXTER INTERNATIONAL INC

US PATENT NO 5 206 269

1800

1600

1400

1200

1000

800

600

400